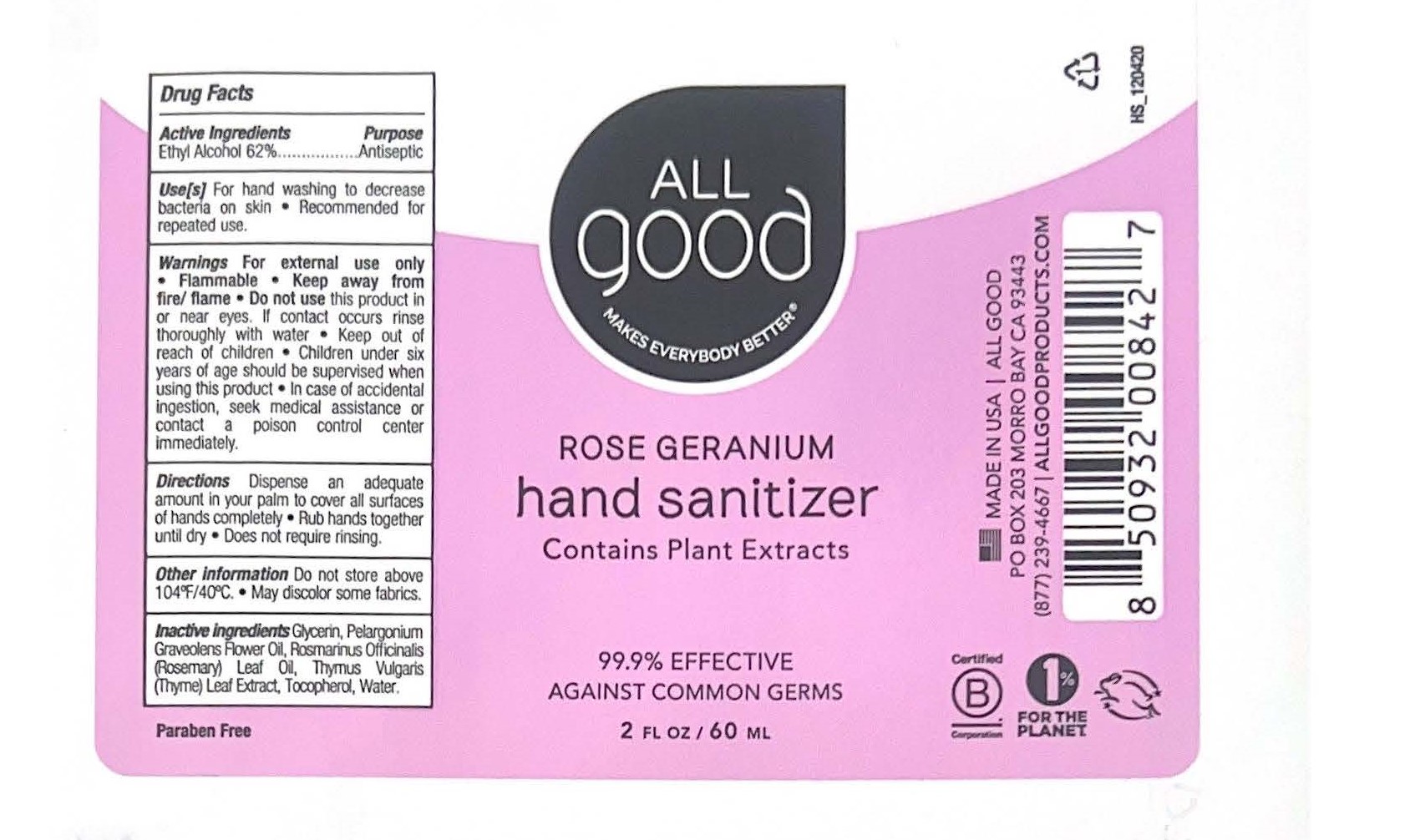 DRUG LABEL: All Good Rose Geranium Hand Sanitizer
NDC: 75786-336 | Form: SPRAY
Manufacturer: Elemental Herbs, Inc.
Category: otc | Type: HUMAN OTC DRUG LABEL
Date: 20241220

ACTIVE INGREDIENTS: ALCOHOL 62 mL/100 mL
INACTIVE INGREDIENTS: WATER; THYMUS VULGARIS LEAF; TOCOPHEROL; GLYCERIN; PELARGONIUM GRAVEOLENS FLOWER OIL; ROSEMARY OIL

All Good - Rose Geranium Hand Sanitizer Spray (11-SP-116)

Active Ingredients

Ethyl Alcohol 62%

Purpose

Antiseptic

Uses

For hand washing to decrease bacteria on the skin. Recommended for repeated use.

Warnings

For external use only. Flammable. Keep away from fire/flame. Do not use this product in or near eyes. If contact occurs rinse thoroughly with water. Keep out of reach of children. Children under six years of age should be supervised when using this product. In case of accidental ingestion, seek medical assistance or contact a poison control center immediately.

Keep out of reach of children. Children under six years of age should be supervised when using this product.

Directions

Dispense an adequate amound in your palm to cover all surfaces of hands completely. Rub hands together until dry. Does not require rinsing.

Other Information

Do not store above 104°C/40°F. May discolor some fabrics.

Inactive Ingredients

Glycerin, Pelargonium Graveolens Flower Oil, Rosmarinus Officinalis (Rosemary) Leaf Oil, Thymus Vulgaris (Thyme) Leaf Extract, Tocopherol, Water